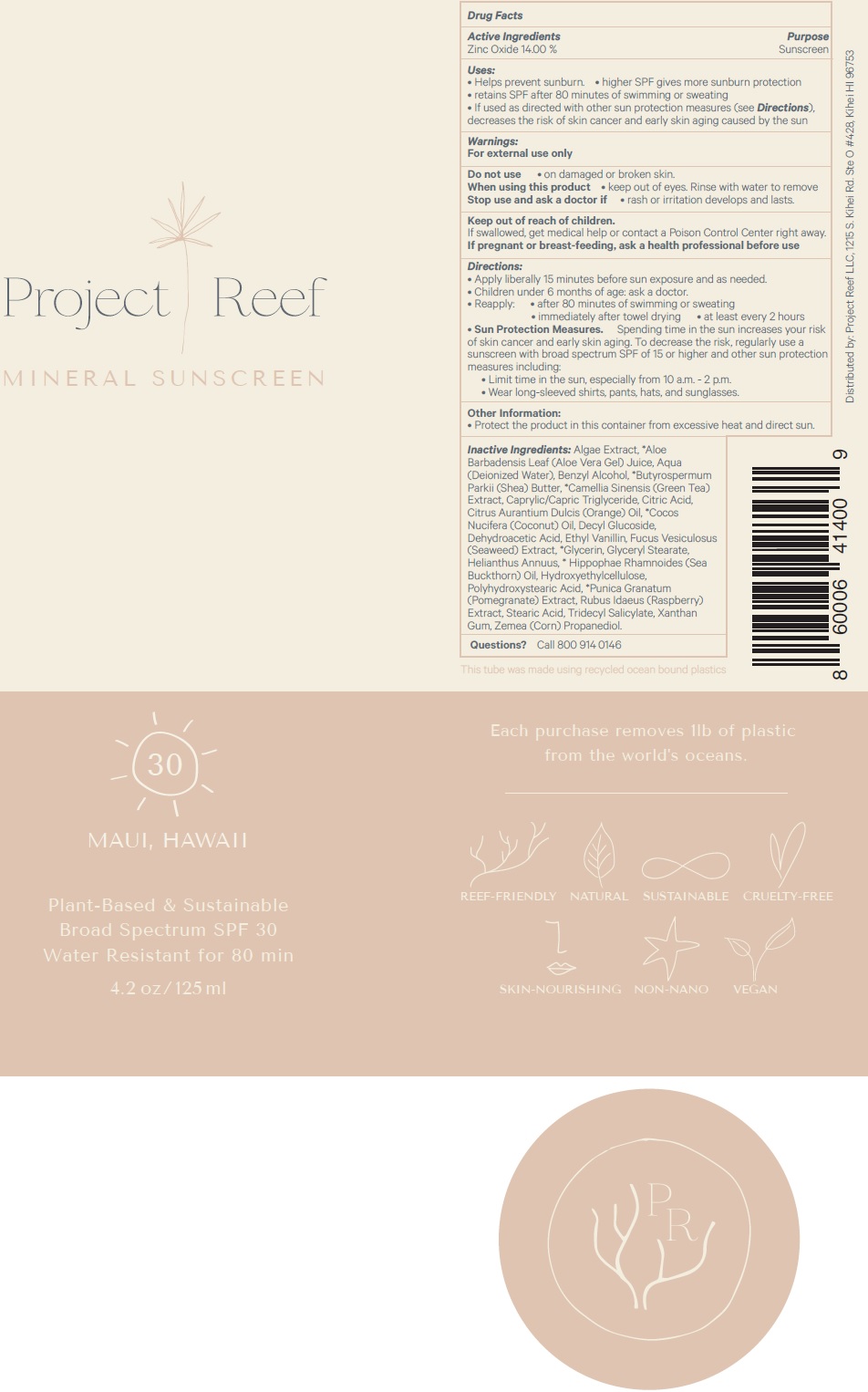 DRUG LABEL: PROJECT REEF SPF-30 Mineral Sunscreen
NDC: 81637-139 | Form: CREAM
Manufacturer: Project Reef LLC
Category: otc | Type: HUMAN OTC DRUG LABEL
Date: 20260119

ACTIVE INGREDIENTS: ZINC OXIDE 140 mg/1 mL
INACTIVE INGREDIENTS: ALOE VERA LEAF; WATER; BENZYL ALCOHOL; SHEA BUTTER; GREEN TEA LEAF; MEDIUM-CHAIN TRIGLYCERIDES; CITRIC ACID MONOHYDRATE; ORANGE OIL; COCONUT OIL; DECYL GLUCOSIDE; DEHYDROACETIC ACID; ETHYL VANILLIN; NORI; GLYCERIN; GLYCERYL MONOSTEARATE; HELIANTHUS ANNUUS FLOWERING TOP; HIPPOPHAE RHAMNOIDES SEED OIL; HYDROXYETHYL CELLULOSE, UNSPECIFIED; POMEGRANATE; RUBUS IDAEUS SEED; STEARIC ACID; TRIDECYL SALICYLATE; XANTHAN GUM; CORN

PROJECT REEF SPF-30 Mineral Sunscreen

Active Ingredients

Zinc Oxide 14.00%

Purpose

Sunscreen

Uses:

- Helps prevent sunburn
- higher SPF gives more sunburn protection
- retains SPF after 80 minutes of swimming or sweating
- If used as directed with other sun protection measures (see), decreases the risk of skin cancer and early skin aging caused by the sun. Directions

Warnings:

For external use only

Do not use

- on damaged or broken skin.

When using this product

- keep out of eyes. Rinse with water to remove.

Stop use and ask a doctor if

- rash or irritation develops and lasts.

Keep out of reach of children.

If swallowed, get medical help or contact a Poison Control Center right away.

If pregnant or breast-feeding,

ask a health professional before use.

Directions:

- Apply liberally 15 minutes before sun exposure and as needed.
- Children under 6 months of age: ask a doctor
- Reapply:
- after 80 minutes of swimming or sweating
- immediately after towel drying
- at least every 2 hours
- Spending time in the sun increases your risk of skin cancer and early skin aging. To decrease risk, regularly use a sunscreen with a Broad Spectrum SPF value of 15 or higher and other sun protection measures including:: Sun Protection Measures.
- Limit time in the sun, especially from 10 a.m. - 2 p.m.
- Wear long- sleeved shirts, pants, hats, and sunglasses

Other Information:

- Protect the product in this container from excessive heat and direct sun.

Inactive Ingredients:

Algae Extract, *Aloe Barbadensis Leaf (Aloe Vera Gel) Juice, Aqua (Deionized Water), Benzyl Alcohol, *Butyrospermum Parkii (Shea) Butter, *Camellia Sinensis (Green Tea) Extract, Caprylic/Capric Triglyceride, Citric Acid, Citrus Aurantium Dulcis (Orange) Oil, *Cocos Nucifera (Coconut) Oil, Decyl Glucoside, Dehydroacetic Acid, Ethyl Vanillin, Fucus Vesiculosus (Seaweed) Extract, *Glycerin, Glyceryl Stearate, Helianthus Annuus, * Hippophae Rhamnoides (Sea Buckthorn) Oil, Hydroxyethylcellulose, Polyhydroxystearic Acid, *Punica Granatum (Pomegranate) Extract, Rubus Idaeus (Raspberry) Extract, Stearic Acid, Tridecyl Salicylate, Xanthan Gum, Zemea (Corn) Propanediol.

Questions?

Call 800 914 0146